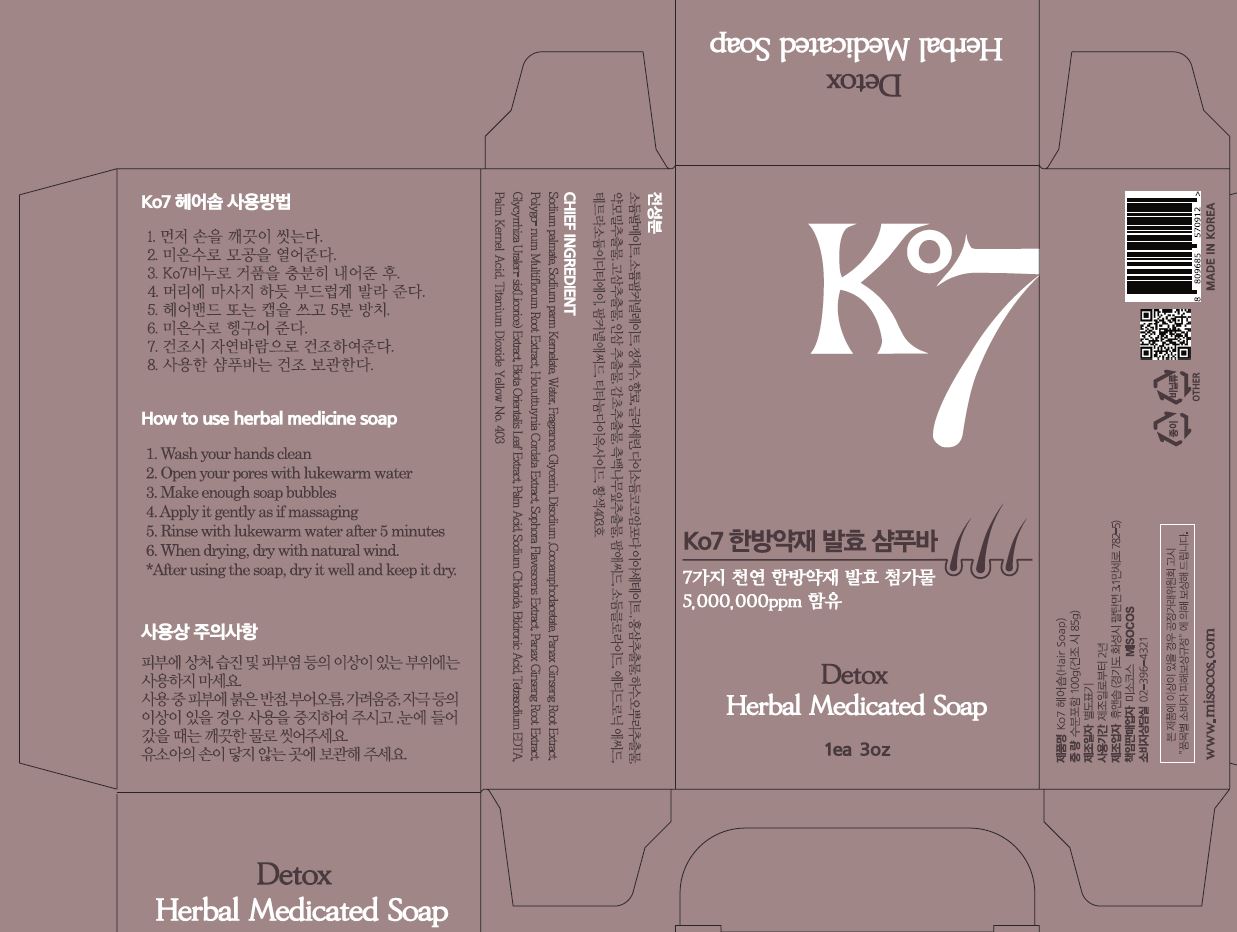 DRUG LABEL: ko7 Herbal MedicatedSoap
NDC: 73466-0009 | Form: SOAP
Manufacturer: MISOCOS
Category: otc | Type: HUMAN OTC DRUG LABEL
Date: 20231015

ACTIVE INGREDIENTS: PANAX GINSENG ROOT OIL 0.3 g/100 g
INACTIVE INGREDIENTS: SODIUM PALM KERNELATE 16.1986 g/100 g; WATER; GLYCERIN

ACTIVE INGREDIENT

Sodium palm kernelate, Panax Ginseng Root Extract

PURPOSE

skin protectant

KEEP OUT OF REACH OF THE CHILDREN

WARNINGS

■ For external use only.

■ Do not use in eyes.

■ lf swallowed, get medical help promptly.

■ Stop use, ask doctor lf irritation occurs.

■ Keep out of reach of children.

DOSAGE AND ADMINISTRATION

for external use only

INACTIVE INGREDIENT

Sodium palm Kernelate, Water, Fragrance, Glycerin,

Disodium-Cocoaphodiacetate, Panax Ginseng Root Extract,Polygonum Multiflorum

Root Extract, Houuttuynia Cordata Extract, Sophora Flavescens Extract. Panax

Ginseng Root Extract, Glycyrrhiza Uralensis(licorice) Extract, Boita Orientalis Leaf

Extract, Palm Acid, Sodium Chloride, Etidronic Acid, Tetrasodium EDTA,

Palm Kernel Acid, Titanium Dioxide Yellow No.403

INDICATIONS AND USAGE

please refer to 'how to use' on the label